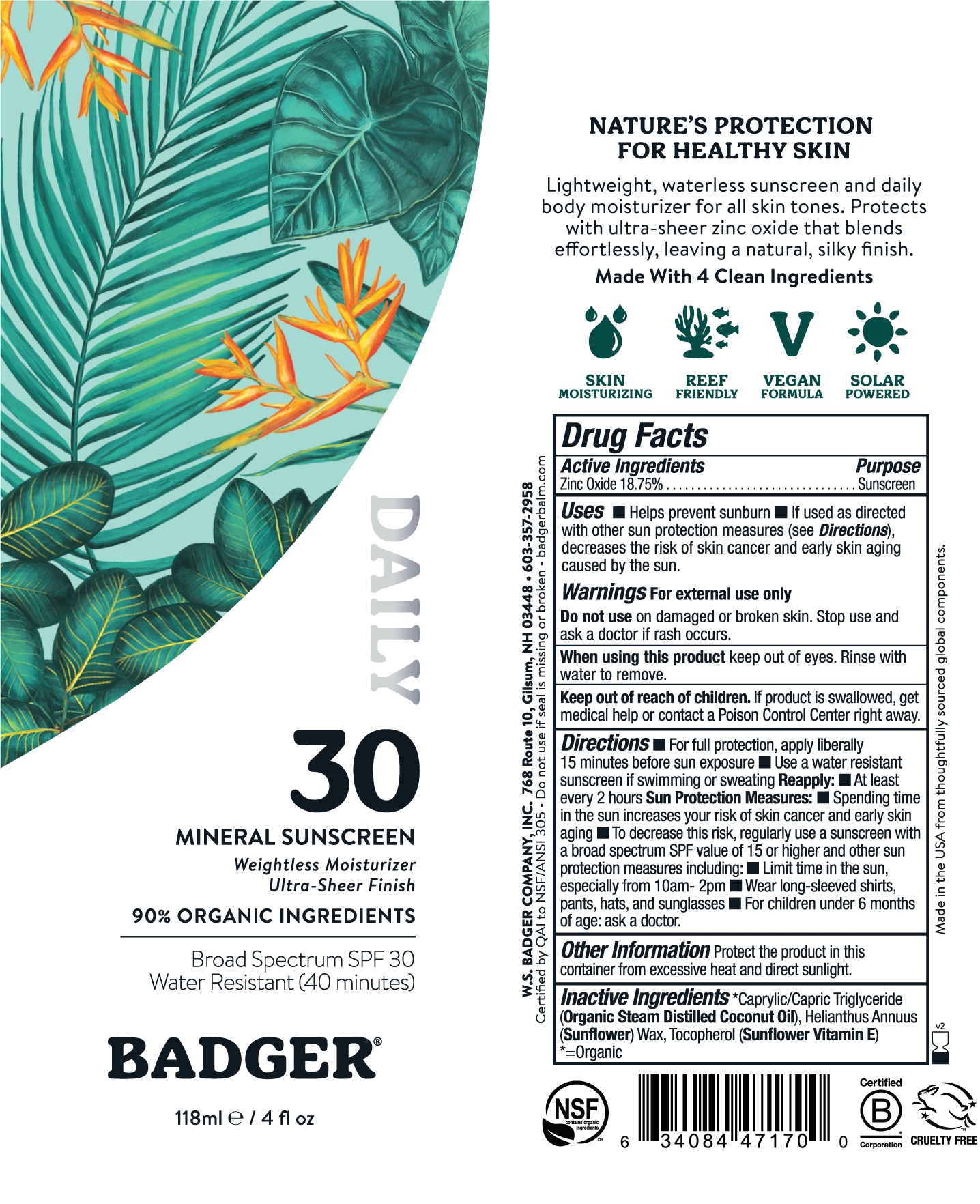 DRUG LABEL: Badger SPF 30 Daily Sunscreen
NDC: 62206-3081 | Form: CREAM
Manufacturer: W.S. Badger Company, Inc.
Category: otc | Type: HUMAN OTC DRUG LABEL
Date: 20241231

ACTIVE INGREDIENTS: ZINC OXIDE 18.75 g/100 mL
INACTIVE INGREDIENTS: MEDIUM-CHAIN TRIGLYCERIDES; HELIANTHUS ANNUUS SEED WAX; TOCOPHEROL

Badger® SPF 30 Daily Mineral Sunscreen

Drug Facts

Active Ingredient

Uncoated Zinc Oxide 18.75%

Purpose

Sunscreen

Uses

- Helps prevent sunburn
- If used as directed with other sun protection measures (see Directions), decreases the risk of skin cancer and early skin aging caused by the sun.

Warnings

For external use only

Do not use on damaged or broken skin. Stop use and ask a doctor if rash occurs.

When using this product keep out of eyes. Rinse with water to remove.

Keep out of reach of children. If product is swallowed, get medical help or contact a Poison Control Center right away.

Directions

- For full protection, apply liberally15 minutes before sun exposure
- Use a water resistant sunscreen if swimming or sweating

Reapply:

- At least every 2 hours

Sun Protection Measures:

- Spending time in the sun increases your risk of skin cancer and early skin aging
- To decrease this risk, regularly use a sunscreen with a broad spectrum SPF value of 15 or higher and other sun protection measures including:
  - Limit time in the sun, especially from 10am-2pm
  - Wear long-sleeved shirts, pants, hats, and sunglasses
- For children under 6 months of age: ask a doctor.

Ingredients

[= Organic] , Tocopherol (Sunflower Vitamin E)

Other Information

Protect the product in this container from excessive heat and direct sunlight.

Recent Major Changes

section heading: Uses

date change incorporated: 02/2024

section heading: Disage and Administration

date change incorporated: 02/2024

PRINCIPAL DISPLAY PANEL - 118 ml Tube Label

BADGER ®

Mineral Sunscreen Cream
Daily

30

Weightless Moisturizer

Ultra-Sheer Finish

90% Organic Ingredients

Broad Spectrum SPF 30

Water Resistant (40 minutes)
NATURE'S PROTECTION FOR HEALTHY SKIN

Lightweight, waterless sunscreen and daily body moisturizer for all skin tones.

Protects with ultra-sheer zinc oxide that blends effortlessly, leaving a natural. silky finish.

Made with 4 Clean Ingredients

Skin Moisturizing

Reef Friendly

Vegan Formula

Solar Powered

NSF

Certified B Corporation

Cruelty Free

118ml / 4 fl.oz